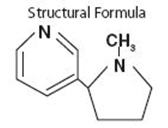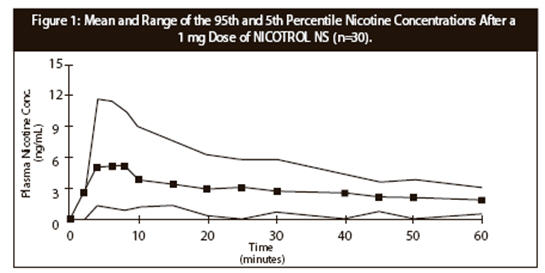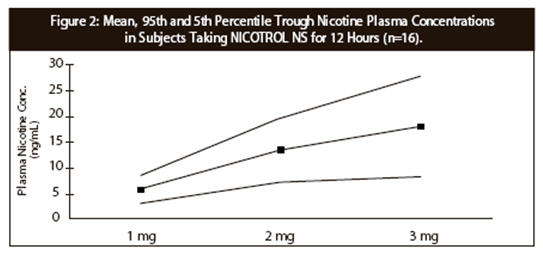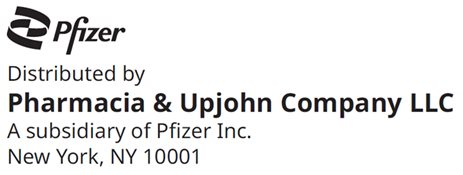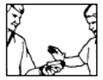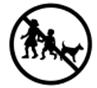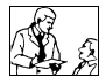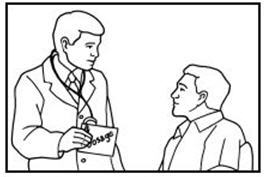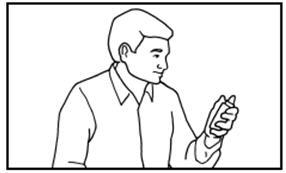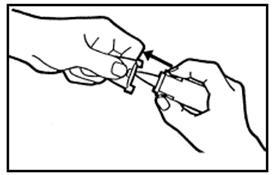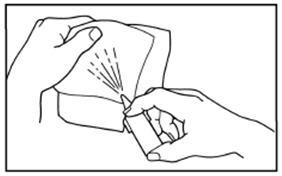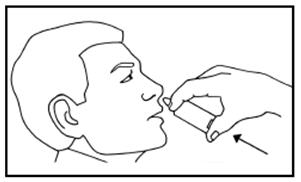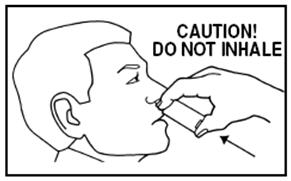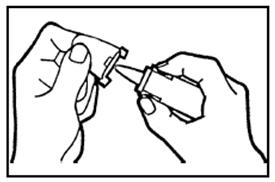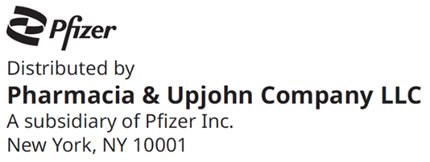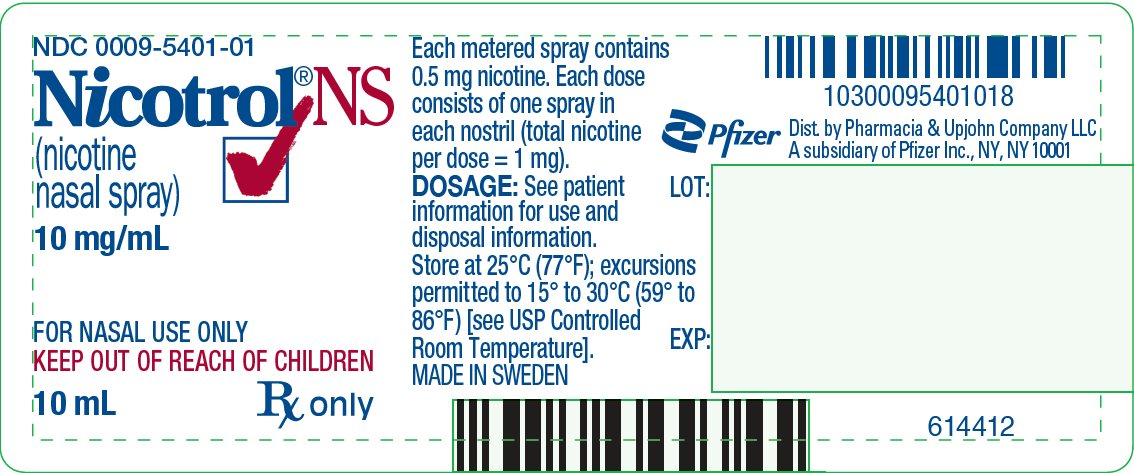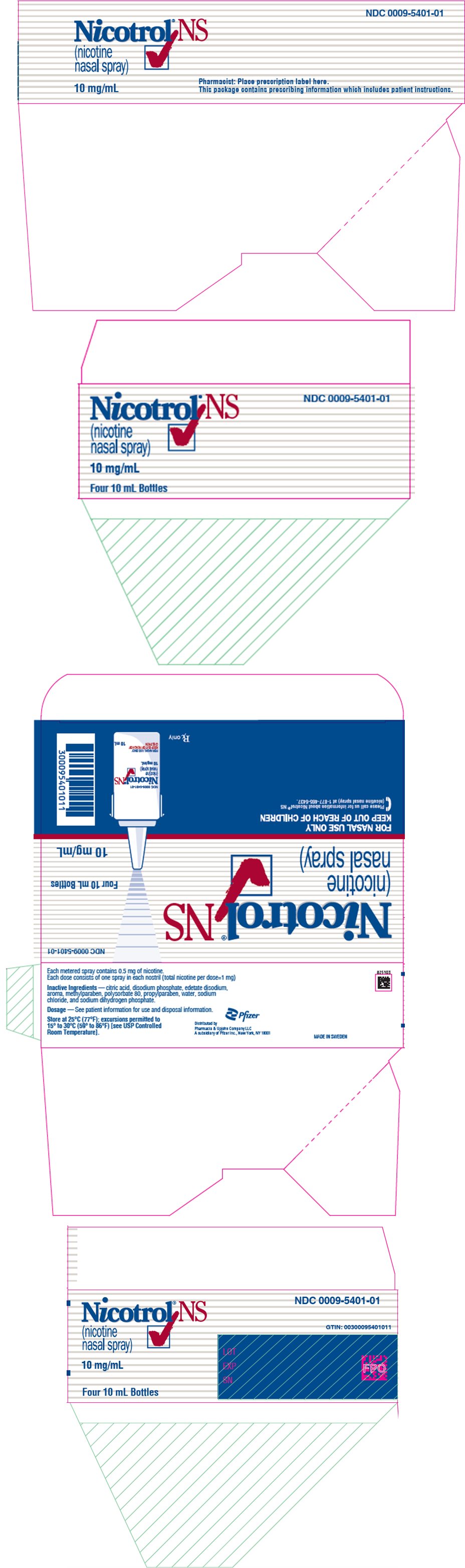 DRUG LABEL: Nicotrol
NDC: 0009-5401 | Form: SPRAY, METERED
Manufacturer: Pharmacia & Upjohn Company LLC
Category: prescription | Type: HUMAN PRESCRIPTION DRUG LABEL
Date: 20250529

ACTIVE INGREDIENTS: NICOTINE 10 mg/1 mL
INACTIVE INGREDIENTS: SODIUM PHOSPHATE, MONOBASIC, UNSPECIFIED FORM; CITRIC ACID MONOHYDRATE; METHYLPARABEN; PROPYLPARABEN; EDETATE DISODIUM; SODIUM CHLORIDE; POLYSORBATE 80; WATER

Nicotrol®NS
(nicotine nasal spray)

10 mg/mL

DESCRIPTION

NICOTROL® NS (nicotine nasal spray) is an aqueous solution of nicotine intended for administration as a metered spray to the nasal mucosa.

Nicotine is a tertiary amine composed of pyridine and a pyrrolidine ring. It is a colorless to pale yellow, freely water-soluble, strongly alkaline, oily, volatile, hygroscopic liquid obtained from the tobacco plant. Nicotine has a characteristic pungent odor and turns brown on exposure to air or light. Of its two stereoisomers, S(-)nicotine is the more active. It is the prevalent form in tobacco and is the form in NICOTROL NS. The free alkaloid is absorbed rapidly through skin, mucous membranes, and the respiratory tract.

Chemical Name: S-3-(1-methyl-2-pyrrolidinyl) pyridine

Molecular Formula: C10H14N2

Molecular Weight: 162.23

Ionization Constants: pKa1 = 7.84, pKa2 = 3.04 at 15°C

Octanol-Water Partition Coefficient: 15:1 at pH 7

Each 10 mL spray bottle contains 100 mg nicotine (10 mg/mL) in an inactive vehicle containing disodium phosphate, sodium dihydrogen phosphate, citric acid, methylparaben, propylparaben, edetate disodium, sodium chloride, polysorbate 80, aroma and water. The solution is isotonic with a pH of 7. It contains no chlorofluorocarbons.

After priming the delivery system for NICOTROL NS, each actuation of the unit delivers a metered dose spray containing approximately 0.5 mg of nicotine. The size of the droplets produced by the unit is in excess of 8 microns. One NICOTROL NS unit delivers approximately 200 applications.

CLINICAL PHARMACOLOGY

Pharmacologic Action

Nicotine, the chief alkaloid in tobacco products, binds stereo-selectively to nicotinic-cholinergic receptors at the autonomic ganglia, in the adrenal medulla, at neuromuscular junctions, and in the brain. Two types of central nervous system effects are believed to be the basis of nicotine's positively reinforcing properties. A stimulating effect is exerted mainly in the cortex via the locus ceruleus and a reward effect is exerted in the limbic system. At low doses, the stimulant effects predominate while at high doses the reward effects predominate. Intermittent intravenous administration of nicotine activates neurohormonal pathways, releasing acetylcholine, norepinephrine, dopamine, serotonin, vasopressin, beta-endorphin, growth hormone, and ACTH.

Pharmacodynamics

The cardiovascular effects of nicotine include peripheral vasoconstriction, tachycardia, and elevated blood pressure. Acute and chronic tolerance to nicotine develops from smoking tobacco or ingesting nicotine preparations. Acute tolerance (a reduction in response for a given dose) develops rapidly (less than 1 hour), but not at the same rate for different physiologic effects (skin temperature, heart rate, subjective effects). Withdrawal symptoms such as cigarette craving can be reduced in most individuals by plasma nicotine levels lower than those from smoking.

Withdrawal from nicotine in addicted individuals can be characterized by craving, nervousness, restlessness, irritability, mood lability, anxiety, drowsiness, sleep disturbances, impaired concentration, increased appetite, minor somatic complaints (headache, myalgia, constipation, fatigue), and weight gain. Nicotine toxicity is characterized by nausea, abdominal pain, vomiting, diarrhea, diaphoresis, flushing, dizziness, disturbed hearing and vision, confusion, weakness, palpitations, altered respiration and hypotension.

Both smoking and nicotine can increase circulating cortisol and catecholamines, and tolerance does not develop to the catecholamine-releasing effects of nicotine. Changes in the response to a concomitantly administered adrenergic agonist or antagonist should be watched for when nicotine intake is altered during NICOTROL NS therapy and/or smoking cessation (See PRECAUTIONS, Drug Interactions).

Pharmacokinetics

Each actuation of NICOTROL NS delivers a metered 50 microliter spray containing approximately 0.5 mg of nicotine. One dose is considered 1 mg of nicotine (2 sprays, one in each nostril).

Absorption

Following administration of 2 sprays of NICOTROL NS approximately 53% ± 16% (Mean ± SD) enters the systemic circulation. No significant difference in rate or extent of absorption could be seen due to the deposition of nicotine on different parts of the nasal mucosa. Plasma concentrations of nicotine obtained from 1 dose (1 mg nicotine) of NICOTROL NS rise rapidly, reaching maximum venous concentrations of 2–12 ng/mL in 4–15 minutes. The apparent absorption half-life of nicotine is approximately 3 minutes. There is wide variation among subjects in their plasma nicotine concentrations from the spray. As a result, after a 1 mg dose of spray approximately 20% of the subjects reached peak nicotine concentrations similar to those seen after smoking one cigarette (7–17 ng/mL) (See DRUG ABUSE AND DEPENDENCE). Figure 1 below plots the mean and 5th and 95th percentile nicotine concentrations after a 1 mg single dose of the nasal spray (n=30).

Table 1: Trough Plasma Nicotine Concentrations after 11 Hours of Dosing With 1 mg, 2 mg and 3 mg of NICOTROL NS per hour (n=16).
Dose | Mean (ng/mL) ± SD | (Range)
1 mg every 60 minutes (1 mg/hr) | 6 ± 3 | (1.7–12)
1 mg every 30 minutes (2 mg/hr) | 14 ± 6 | (1.5–24)
1 mg every 20 minutes (3 mg/hr) | 18 ± 10 | (1.2–35)

The data from Table 1 is derived from a three-way cross-over study of repeated applications of NICOTROL NS in sixteen smokers (8 male, 8 female) ranging in age from 18 to 48 years. There is a slight deviation from dose-concentration proportionality from one dose to three doses of NICOTROL NS per hour as shown in Figure 2.

Sixteen smokers (7 males and 9 females) ranging in age from 22 to 44 years were dosed with 1 mg of NICOTROL NS every hour for 10 hours. The pharmacokinetic parameters that were obtained are presented in Table 2.

Table 2: Nicotine Pharmacokinetic Parameters at Steady-State for 1 mg/hour of NICOTROL NS Administered Hourly for Ten Hours (Mean ± SD and Range), (n=16).
Parameter | 1 mg (2 sprays) | (Range)
Cavg (ng/mL) | 8 ± 3 | (2.5–12)
Cmax (ng/mL) | 9 ± 3 | (3.1–14)
Tmax (minutes) | 13 ± 5 | (10–20)
Cavg: average plasma nicotine concentration for the dosing interval of 10–11 hours
Cmax: maximum measured plasma concentration after last dose administration
Tmax: time of maximum plasma concentration after last dose administration

Distribution

The volume of distribution following IV administration of nicotine is approximately 2 to 3 L/kg. Plasma protein binding of nicotine is <5%. Therefore, changes in nicotine binding from use of concomitant drugs or alterations of plasma proteins by disease states would not be expected to have significant effects on nicotine kinetics.

Metabolism

More than 20 metabolites of nicotine have been identified, all of which are less active than the parent compound. The primary urinary metabolites are cotinine (15% of the dose) and trans-3-hydroxycotinine (45% of the dose). Cotinine has a half-life of 15 to 20 hours and concentrations that exceed nicotine by 10-fold. The major site for the metabolism of nicotine is the liver. The kidney and lung are also sites of nicotine metabolism.

Elimination

About 10% of the nicotine absorbed is excreted unchanged in the urine. This may be increased to up to 30% with high urine flow rates and urinary acidification below pH 5. The average plasma clearance is about 1.2 L/min in a healthy adult smoker. The apparent elimination half-life of nicotine from NICOTROL NS is 1 to 2 hours.

Pharmacokinetic Model

The data were well described by a two-compartment model with first-order input.

Based on individual fits (N=18) the following parameters were derived after the administration of a 1 mg dose: Absorption rate constant (Ka) = 14.4 ± 7.3 hr^-1 (Mean ± SD), Elimination rate constant (Ke) = 0.60 ± 0.53 hr^-1, Distribution rate constants (K12) = 4.84 ± 2.57 hr^-1, (K21) = 4.35 ± 2.30 hr^-1, Volume of distribution over fraction absorbed (V/F) = 2.73 ± 0.82 L/kg in 8 female and 10 male adults weighing 76 ± 15 kg.

Gender Differences

Intersubject variability (50% coefficient of variation) among the pharmacokinetic parameters (AUC, Cmax and Clearance/kg) were observed for both genders. There were no differences between females or males in the kinetics of NICOTROL NS.

Renal Impairment

Progressive severity of renal impairment is associated with decreased total clearance of nicotine. Nicotine clearance was decreased by 30% on average in subjects with moderate renal impairment and 50% on average in subjects with severe renal impairment.

Hepatic Impairment

In smokers with liver cirrhosis but only mild impairment of hepatic function (Child-Pugh score 5), the pharmacokinetics of nicotine is unaffected. However, in smokers with moderately impaired liver function (Child-Pugh score 7), total clearance has been reported to be reduced on average by 40-50%. There are no data about the pharmacokinetics of nicotine in smokers with a Child-Pugh score exceeding 7, but these subjects are expected to show similar or greater effects on clearance of nicotine as patients with moderately impaired liver function.

Drug/Drug Interactions

The extent of absorption is slightly reduced (approximately 10%) in patients with the common cold/rhinitis. In patients with rhinitis the peak plasma concentration is reduced by approximately 20% (concentrations are lower by 1.5 ng/mL on average) and the time to peak concentration prolonged by approximately 30% (delayed by 7 minutes on average). The use of a nasal vasoconstrictor such as xylometazoline in patients with rhinitis will further prolong the time to peak by approximately 40% (delayed by 15 minutes on average), but the peak plasma concentration remains on average the same as those with rhinitis.

CLINICAL TRIALS

The efficacy of NICOTROL NS therapy as an aid to smoking cessation was demonstrated in three single-center, placebo-controlled, double-blind trials with a total of 730 patients. One of the trials used NICOTROL NS with individual counseling while the other two used group support. Patients with severe or symptomatic cardiovascular disease, hypertension, asthma, diabetes or severe allergy were not included in the studies. The amount of NICOTROL NS used was left to the discretion of each patient, with a minimum dose of 8 mg/day and a maximum dose of 40 mg/day.

In all three studies, the recommended duration of treatment was 3 months; however in two of these trials, 241 patients were permitted to continue to use the product for up to 1 year, if they wished. Among the 64 patients abstinent from cigarettes at the end of a year, 23 (36%) were still using the spray, and probable dependence on the spray was seen in several patients (See DRUG ABUSE AND DEPENDENCE).

Quitting was defined as total abstinence from smoking for at least 4 weeks. The "quit rates" are the percentage of all persons initially enrolled who continuously abstained after week 2 or 4.

In all three studies, NICOTROL NS was more effective than placebo at 6 weeks, 3 months, 6 months, and 1 year. The two studies where NICOTROL NS could be used for more than 6 months did not have a better outcome at 1 year than the study in which NICOTROL NS was discontinued at 6 months.

Table 3: Quit Rates by Treatment (N=730 smokers in 3 Studies)
Group | Size (n) | At 6 Weeks | At 3 Months | At 6 Months | At 1 Year
NICOTROL NS | 369 | 49–58% | 41–45% | 31–35% | 23–27%
Placebo | 361 | 21–32% | 17–20% | 12–15% | 10–15%

Patients treated with NICOTROL NS had more relief of the urge to smoke and withdrawal symptoms compared with placebo-treated patients.

NICOTROL NS allows the patient to vary the dose of nicotine on a short-term basis. As with other variable dose smoking cessation products, NICOTROL NS may be useful in the management of highly dependent smokers.

INDICATIONS AND USAGE

NICOTROL NS is indicated as an aid to smoking cessation for the relief of nicotine withdrawal symptoms. NICOTROL NS therapy should be used as a part of a comprehensive behavioral smoking cessation program.

The safety and efficacy of the continued use of NICOTROL NS for periods longer than 6 months have not been adequately studied and such use is not recommended.

CONTRAINDICATIONS

Use of NICOTROL NS therapy is contraindicated in patients with known hypersensitivity or allergy to nicotine or to any component of the product.

WARNINGS

Nicotine from any source can be toxic and addictive. Smoking causes lung disease, cancer, and heart disease and may adversely affect pregnant women or the fetus. For any smoker, with or without concomitant disease or pregnancy, the risk of nicotine replacement in a smoking cessation program should be weighed against the hazard of continued smoking, and the likelihood of achieving cessation of smoking without nicotine replacement.

Pregnancy, Warning

Tobacco smoke, which has been shown to be harmful to the fetus, contains nicotine, hydrogen cyanide, and carbon monoxide. Nicotine has been shown in animal studies to cause fetal harm. It is therefore presumed that NICOTROL NS can cause fetal harm when administered to a pregnant woman. The effect of nicotine delivery by NICOTROL NS has not been examined in pregnancy (See PRECAUTIONS, Pregnancy). Therefore, pregnant smokers should be encouraged to attempt cessation using educational and behavioral interventions before using pharmacological approaches. If NICOTROL NS is used during pregnancy, or if the patient becomes pregnant while using it, the patient should be apprised of the potential hazard to the fetus.

Safety Note Concerning Children

The amounts of nicotine that are tolerated by adult smokers can produce signs and symptoms of poisoning and could prove fatal if NICOTROL NS is used or ingested by children or pets. Suspected nicotine poisoning in a child should be considered a medical emergency and treated immediately. A full bottle of NICOTROL NS contains 100 mg of nicotine, some of which will still be in the bottle when it is discarded. Therefore, patients should be cautioned to keep both used and unused containers of NICOTROL NS out of the reach of children and pets.

PRECAUTIONS

General

The patient should be urged to stop smoking completely when initiating NICOTROL NS therapy (See DOSAGE AND ADMINISTRATION). Patients should be informed that if they continue to smoke while using the product, they may experience adverse effects due to peak nicotine levels higher than those experienced from smoking alone. If there is a clinically significant increase in cardiovascular or other effects attributable to nicotine, the treatment should be discontinued (See WARNINGS). Physicians should anticipate that concomitant medications may need dosage adjustment (See Drug Interactions).

Sustained use (beyond 6 months) of NICOTROL NS by patients who stop smoking is not recommended and should be discouraged (See DRUG ABUSE AND DEPENDENCE).

Care should be taken not to spray the eyes while administering NICOTROL NS.

Asthma, Bronchospasm and Reactive Airway Disease

Exacerbation of bronchospasm in patients with pre-existing asthma has been reported. Use of NICOTROL NS in patients with severe reactive airway disease is not recommended. In a small clinical study of 33 subjects, use of NICOTROL NS by smokers with chronic rhinitis and sinusitis was associated with irritant effects with no significant impairment in nasal condition.

Effect of NICOTROL NS on the Nasal Mucosa

Topical application of either nicotine or tobacco products is irritating to the nasal mucosa and physicians should consider both the risks and benefits to the patient before initiating or continuing NICOTROL NS therapy.

The effect of NICOTROL NS on the nasal mucosa was studied in 39 cigarette smokers who used NICOTROL NS for 1 month. When compared to baseline, random biopsies taken after four weeks of treatment revealed 1 patient with persistence of pre-existing dysplasia and 1 patient with a newly found dysplasia. In both, dysplasia was not seen after a recovery period of eight weeks.

Forty-two patients who used NICOTROL NS for more than 6 months underwent follow-up ear, nose and throat examinations 1 to 3 months after discontinuing the use of the spray. Many reported local irritant effects of the spray during spray use, but none showed persistent mucosal injury that the examining physician could attribute to use of the product.

The clinical significance of these findings is not known, but extended use of the product beyond six months is not recommended.

Cardiovascular or Peripheral Vascular Diseases

The risks of nicotine replacement in patients with cardiovascular and peripheral vascular diseases should be weighed against the benefits of including nicotine replacement in a smoking cessation program for them. Specifically, patients with coronary heart disease (history of myocardial infarction and/or angina pectoris), serious cardiac arrhythmias, or vasospastic diseases (Buerger's disease, Prinzmetal's variant angina and Raynaud's phenomena) should be evaluated carefully before nicotine replacement is prescribed.

Tachycardia occurring in association with nicotine replacement therapy has been reported. No serious cardiovascular events were reported in clinical studies with NICOTROL NS, but if symptoms occur, its use should be discontinued.

NICOTROL NS generally should not be used in patients during the immediate post myocardial infarction period, nor in patients with serious arrhythmias, or with severe or worsening angina.

Renal or Hepatic Insufficiency

Pharmacokinetic studies in patients with moderate to severe renal impairment or moderate to severe hepatic impairment have shown decreased nicotine clearance. The pharmacokinetics of nicotine have not been studied in the elderly. Given that nicotine is extensively metabolized and that its total system clearance is dependent on liver blood flow, some influence of hepatic impairment on drug kinetics (reduced clearance with potential for increased adverse effects) are anticipated. Moderate and severe renal impairment would be expected to affect the clearance of nicotine or its metabolites from the circulation (See PHARMACOKINETICS). Consider dose reduction and monitoring patients for adverse events (such as nausea or dizziness) associated with elevated levels of nicotine.

Endocrine Diseases

NICOTROL NS therapy should be used with caution in patients with hyperthyroidism, pheochromocytoma or insulin-dependent diabetes, since nicotine causes the release of catecholamines by the adrenal medulla.

Peptic Ulcer Disease

Nicotine delays healing in peptic ulcer disease; therefore, NICOTROL NS therapy should be used with caution in patients with esophagitis, active gastric or peptic ulcers and only when the benefits of including nicotine replacement in a smoking cessation program outweigh the risks.

Accelerated Hypertension

Nicotine therapy constitutes a risk factor for development of malignant hypertension in patients with accelerated hypertension; therefore, NICOTROL NS therapy should be used with caution in these patients and only when the benefits of including nicotine replacement in a smoking cessation program outweigh the risks.

Information To Patient

A patient instruction sheet is included in the package of NICOTROL NS dispensed to the patient. Patients should be encouraged to read the instruction sheet carefully and to ask their physician and pharmacist about the proper use of the product (See DOSAGE AND ADMINISTRATION).

It should be explained to patients that they are likely to experience nasal irritation, which may become less bothersome with continued use.

Patients must be advised to keep both used and unused containers out of the reach of children and pets.

Drug Interactions

The extent of absorption and peak plasma concentration is slightly reduced in patients with the common cold/rhinitis. In addition, the time to peak concentration is prolonged. The use of a nasal vasoconstrictor such as xylometazoline in patients with rhinitis will further prolong the time to peak (See PHARMACOKINETICS). Smoking cessation, with or without nicotine replacement, may alter the pharmacokinetics of certain concomitant medications.

May Require a Decrease in Dose at Cessation of Smoking | Possible Mechanism
Acetaminophen, caffeine, imipramine, oxazepam, pentazocine, propranolol, or other beta-blockers, theophylline | Deinduction of hepatic enzymes on smoking cessation.
Insulin | Increase of subcutaneous insulin absorption with smoking cessation.
Adrenergic antagonists (e.g. prazosin, labetalol) | Decrease in circulating catecholamines with smoking cessation.
May Require an Increase in Dose at Cessation of Smoking | Possible Mechanism
Adrenergic agonists (e.g. isoproterenol, phenylephrine) | Decrease in circulating catecholamines with smoking cessation.

Carcinogenesis, Mutagenesis, Impairment Of Fertility

Nicotine itself does not appear to be a carcinogen in laboratory animals. However, nicotine and its metabolites increased the incidences of tumors in the cheek pouches of hamsters and forestomach of F344 rats, respectively, when given in combination with tumor-initiators. One study, which could not be replicated, suggested that cotinine, the primary metabolite of nicotine, may cause lymphoreticular sarcoma in the large intestine of rats.

Neither nicotine nor cotinine were mutagenic in the Ames salmonella test. Nicotine-induced repairable DNA damage in an E. coli test system. Nicotine was shown to be genotoxic in a test system using Chinese hamster ovary cells. In rats and rabbits, implantation can be delayed or inhibited by a reduction in DNA synthesis that appears to be caused by nicotine. Studies have shown a decrease in litter size in rats treated with nicotine during gestation.

Pregnancy

The harmful effects of cigarette smoking on maternal and fetal health are clearly established. These include low birth weight, an increased risk of spontaneous abortion, and increased perinatal mortality. The specific effects of NICOTROL NS on fetal development are unknown. Therefore pregnant smokers should be encouraged to attempt cessation using educational and behavioral interventions before using pharmacological approaches.

Spontaneous abortion during nicotine replacement therapy has been reported; as with smoking, nicotine as a contributing factor cannot be excluded.

NICOTROL NS should be used during pregnancy only if the likelihood of smoking cessation justifies the potential risk of using it by the pregnant patient, who might continue to smoke.

Teratogenicity

Animal Studies

Nicotine was shown to produce skeletal abnormalities in the offspring of mice when toxic doses were given to the dams (25 mg/kg IP or SC).

Human Studies

Nicotine teratogenicity has not been studied in humans except as a component of cigarette smoke (each cigarette smoked delivers about 1 mg of nicotine). It has not been possible to conclude whether cigarette smoking is teratogenic to humans.

Other Effects

Animal Studies

A nicotine bolus (up to 2 mg/kg) to pregnant rhesus monkeys caused acidosis, hypercarbia, and hypotension (fetal and maternal concentrations were about 20 times those achieved after smoking one cigarette in 5 minutes). Fetal breathing movements were reduced in the fetal lamb after intravenous injection of 0.25 mg/kg nicotine to the ewe (equivalent to smoking 1 cigarette every 20 seconds for 5 minutes). Uterine blood flow was reduced about 30% after infusion of 0.1 µg/kg/min nicotine to pregnant rhesus monkeys (equivalent to smoking about six cigarettes every minute for 20 minutes).

Human Experience

Cigarette smoking during pregnancy is associated with an increased risk of spontaneous abortion, low birth weight infants and perinatal mortality. Nicotine and carbon monoxide are considered the most likely mediators of these outcomes. The effects of cigarette smoking on fetal cardiovascular parameters have been studied near term. Cigarettes increased fetal aortic blood flow and heart rate and decreased uterine blood flow and fetal breathing movements. NICOTROL NS has not been studied in pregnant women.

Labor and Delivery

NICOTROL NS is not recommended for use during labor and delivery. The effect of nicotine on a mother or the fetus during labor is unknown.

Use in Nursing Mothers

Caution should be exercised when NICOTROL NS is administered to nursing mothers. The safety of NICOTROL NS therapy in nursing infants has not been examined. Nicotine passes freely into breast milk; the milk to plasma ratio averages 2.9. Nicotine is absorbed orally. An infant has the ability to clear nicotine by hepatic first-pass clearance; however, the efficiency of removal is probably lowest at birth. Nicotine concentrations in milk can be expected to be lower with NICOTROL NS when used as recommended than with cigarette smoking, as maternal plasma nicotine concentrations are generally reduced with nicotine replacement. The risk of exposure of the infant to nicotine from NICOTROL NS therapy should be weighed against the risks associated with the infant's exposure to nicotine from continued smoking by the mother (passive smoke exposure and contamination of breast milk with other components of tobacco smoke) and from NICOTROL NS alone, or in combination with continued smoking.

Pediatric Use

NICOTROL NS therapy is not recommended for use in the pediatric population because its safety and effectiveness in children and adolescents who smoke have not been evaluated.

Geriatric Use

Clinical studies of NICOTROL NS did not include sufficient numbers of subjects age 65 and over to determine whether they respond differently from younger subjects. Other reports on clinical experience have not identified differences between older and younger patients. In general, dosage selection for an elderly patient should be cautious, usually starting at the low end of the dosage range reflecting the greater frequency of decreased hepatic, renal, or cardiac function, and of concomitant disease.

ADVERSE REACTIONS

Assessment of adverse events in the 730 patients who participated in controlled clinical trials is complicated by the occurrence of signs and symptoms of nicotine withdrawal in some patients and nicotine excess in others. The incidence of adverse events is confounded by the many minor complaints that smokers commonly have, by continued smoking by many patients and the local irritation from both active drug and the pepper placebo. No serious adverse events were reported during the trials.

Common Smoker's Complaints

Common complaints experienced by the smokers in the study (users of both active and placebo spray) include: chest tightness, dyspepsia, paresthesia (tingling) in limbs, constipation, and stomatitis.

Tobacco Withdrawal Symptoms

Symptoms of tobacco withdrawal were frequent in users of both active and placebo sprays. Common withdrawal symptoms seen in over 5% of patients included: anxiety, irritability, restlessness, cravings, dizziness, impaired concentration, weight increase, emotional lability, somnolence and fatigue, increased sweating, and insomnia. Less frequently seen probable withdrawal symptoms (under 5%) included: confusion, depression, apathy, tremor, increased appetite, incoordination, and increased dreaming.

Anxiety, irritability, restlessness, and tobacco cravings occurred about equally in both groups, while other symptoms tended to be slightly more common on placebo spray.

Effects of the Spray

NICOTROL NS and the pepper-containing placebo were both associated with irritant side effects on the nasopharyngeal and ocular tissues. During the first 2 days of treatment, nasal irritation was reported by nearly all (94%) of the patients, the majority of whom rated it as either moderate or severe. Both the frequency and severity of nasal irritation declined with continued use of NICOTROL NS but was still experienced by most (81%) of the patients after 3 weeks of treatment, with most patients rating it as moderate or mild.

Other common side effects for both active and placebo groups were: runny nose, throat irritation, watering eyes, sneezing, and coughing.

The following local events were reported somewhat more commonly for active than for placebo spray: nasal congestion, subjective comments related to the taste or use of the dosage form, sinus irritation, transient epistaxis, eye irritation, transient changes in sense of smell, pharyngitis, paresthesia of the nose, mouth or head, numbness of the nose, or mouth, burning of the nose or eyes, earache, facial flushing, transient changes in sense of taste, hoarseness, nasal ulcer or blister.

Effects of Nicotine

Feelings of dependence on the spray were reported by more patients on active spray than placebo. Drug-like effects such as calming were also more frequent on active spray (See DRUG ABUSE AND DEPENDENCE).

Other Adverse Effects

Adverse events which could not be classified and listed above and which were reported by >1% of patients on active spray are listed in the following table:

Adverse Events Not Attributable to Intercurrent Illness

Adverse Event | Active | Placebo
HEADACHE | 18% | 15%
BACK PAIN | 6% | 4%
DYSPNEA | 5% | 6%
NAUSEA | 5% | 5%
ARTHRALGIA | 5% | 1%
MENSTRUAL DISORDER | 4% | 4%
PALPITATION | 4% | 4%
FLATULENCE | 4% | 3%
TOOTH DISORDER | 4% | 1%
GUM PROBLEMS | 4% | 1%
MYALGIA | 3% | 4%
ABDOMINAL PAIN | 3% | 3%
CONFUSION | 3% | 3%
ACNE | 3% | 1%
DYSMENORRHEA | 3% | 0%
PRURITUS | 2% | 3%

Adverse events reported with a frequency of <1% among active spray users are listed below:

Body as a Whole: edema peripheral, pain, numbness, allergy
Gastrointestinal: dry mouth, hiccup, diarrhea
Hematologic: purpura
Neurological: aphasia, amnesia, migraine, numbness
Respiratory: bronchitis, bronchospasm, sputum increased
Skin and appendages: rash, purpura
Special Senses: vision abnormal

Adverse reactions not listed above that have been identified during post-marketing experience with the nicotine nasal spray formulation are listed below:

Gastrointestinal disorders: dysphagia

General disorders and administration site conditions: chest pain

Immune system disorders: anaphylactic reaction

Nervous system disorders: seizure

DRUG ABUSE AND DEPENDENCE

NICOTROL NS has a dependence potential intermediate between other nicotine-based therapies and cigarettes. This is the result of differences between cigarettes, NICOTROL NS, nicotine gum and nicotine patches in pharmacokinetic and dosing characteristics commonly associated with abuse and dependence. NICOTROL NS is distinct from other nicotine-based smoking cessation therapies in its greater speed of onset, greater capacity for self-titration of dose, and frequent and rapid fluctuations in plasma nicotine concentration.

Dependence on nicotine nasal spray occurred in the clinical trials. Feelings of dependency on the spray were reported by 32% of active spray users and 13% of placebo spray users. Such dependence may represent transference of tobacco-related nicotine dependence to NICOTROL NS.

Fifteen to 20% of patients used the active spray for longer periods than recommended (6 months to 1 year) and 5% used the spray at a higher dose than recommended. Some of these patients experienced anxiety about stopping the spray and some reported craving for the spray rather than for cigarettes.

OVERDOSAGE

The oral LD50 for nicotine is >5 mg/kg in dogs and >24 mg/kg in rodents. Death is due to respiratory paralysis. The oral minimum acute lethal dose for nicotine in adult humans is reported to be 40 to 60 mg (<1 mg/kg). A full bottle of NICOTROL NS contains 100 mg of nicotine.

Doses of nicotine that are tolerated by adult smokers during treatment may produce severe signs and symptoms of poisoning in children and may prove fatal. Suspected nicotine poisoning in a child should be considered a medical emergency and treated immediately (See WARNINGS, Safety Note Concerning Children).

NICOTROL NS would be expected to be irritating if sprayed in the eyes, mouth or ears. Eye exposure should be treated with copious irrigation with water for 20 minutes. Large oral nicotine ingestions cause vomiting and the consequences of an overdose will vary; should this occur, patients should contact their physician immediately. For additional emergency information, call your regional poison center.

Signs and Symptoms of Nicotine Toxicity

Signs and symptoms of an overdose of NICOTROL NS would be expected to be the same as those of acute nicotine poisoning including: pallor, cold sweat, nausea, salivation, vomiting, abdominal pain, diarrhea, headache, dizziness, disturbed hearing and vision, tremor, mental confusion, and weakness. Prostration, hypotension, arrhythmia, and respiratory failure may ensue with large overdoses. Lethal doses produce convulsions quickly and death follows as a result of peripheral or central respiratory paralysis or, less frequently, cardiac failure.

Overdose from Ingestion

If emesis has not occurred, it should be induced in conscious patients with a suitable emetic followed by an appropriate dose of activated charcoal. In unconscious patients with a secure airway, instill activated charcoal via a nasogastric tube. A saline cathartic or sorbitol may be added to the first dose of activated charcoal.

Management of Nicotine Poisoning

Administration of nicotine must be stopped immediately and the patient should be treated symptomatically. Other supportive measures include diazepam or barbiturates for seizures, atropine for excessive bronchial secretions or diarrhea, respiratory support for respiratory failure, and vigorous fluid support for hypotension and cardiovascular collapse.

DOSAGE AND ADMINISTRATION

It is important that patients understand the instructions for use of NICOTROL NS, and have their questions answered. They should clearly understand the directions for using NICOTROL NS and safely disposing of the used container. They should be instructed to stop smoking completely when they begin using the product.

Patients should be instructed not to sniff, swallow or inhale through the nose as the spray is being administered. They should also be advised to administer the spray with the head tilted back slightly.

The dose of NICOTROL NS, should be individualized on the basis of each patient's nicotine dependence and the occurrence of symptoms of nicotine excess (See Individualization of Dosage).

Each actuation of NICOTROL NS delivers a metered 50 microliter spray containing 0.5 mg of nicotine. One dose is 1 mg of nicotine (2 sprays, one in each nostril).

Patients should be started with 1 or 2 doses per hour, which may be increased up to a maximum recommended dose of 40 mg (80 sprays, somewhat less than 1/2 bottle) per day. For best results, patients should be encouraged to use at least the recommended minimum of 8 doses per day, as less is unlikely to be effective. In clinical trials, the patients who successfully quit smoking used the product heavily when nicotine withdrawal was at its peak, sometimes up to the recommended maximum of 40 doses per day (in heavier smokers). Dosing recommendations are summarized in Table 4.

Table 4:
Maximum Recommended Duration of Treatment | Recommended Doses per Hour | Maximum Doses per Hour | Maximum Doses per Day
3 months | 1–2 [One dose=2 sprays (one in each nostril). One dose delivers 1 mg of nicotine to the nasal mucosa.] | 5 | 40

No tapering strategy has been shown to be optimal in clinical studies. Many patients simply stopped using the spray at their last clinic visit.

Recommended strategies for discontinuation of use include suggesting that patients: use only 1/2 a dose (1 spray) at a time, use the spray less frequently, keep a tally of daily usage, try to meet a steadily reducing usage target, skip a dose by not medicating every hour, or set a planned "quit date" for stopping use of the spray.

Individualization of Dosage

The success or failure of smoking cessation is influenced by the quality, intensity and frequency of supportive care. Patients are more likely to quit smoking if they are seen frequently and participate in formal smoking cessation programs.

The goal of NICOTROL NS therapy is complete abstinence. If a patient is unable to stop smoking by the fourth week of therapy, treatment should probably be discontinued.

Patients who fail to quit on any attempt may benefit from interventions to improve their chances for success on subsequent attempts. Patients who were unsuccessful should be counseled and should then probably be given a "therapy holiday" before the next attempt. A new quit attempt should be encouraged when conditions are more favorable.

Based on the clinical trials, a reasonable approach to assisting patients in their attempt to quit smoking is to begin initial treatment, using the recommended dosage (See DOSAGE AND ADMINISTRATION). Regular use of the spray during the first week of treatment may help patients adapt to the irritant effects of the spray. Dosage can then be adjusted in those subjects with signs or symptoms of nicotine withdrawal or excess. Patients who are successfully abstinent on NICOTROL NS should be treated at the selected dosage for up to 8 weeks, following which use of the spray should be discontinued over the next 4 to 6 weeks. Some patients may not require gradual reduction of dosage and may abruptly stop treatment successfully. Treatment with NICOTROL NS for longer periods has not been shown to improve outcome, and the safety of use for periods longer than 6 months has not been established.

The symptoms of nicotine withdrawal overlap those of nicotine excess (See CLINICAL PHARMACOLOGY, Pharmacodynamics and ADVERSE REACTIONS). Since patients using NICOTROL NS may also smoke intermittently, it is sometimes difficult to determine if patients are experiencing nicotine withdrawal or nicotine excess. Controlled clinical trials of nicotine products suggest that palpitations, nausea and sweating are more often symptoms of nicotine excess, whereas anxiety, nervousness and irritability are more often symptoms of nicotine withdrawal.

SAFETY AND HANDLING

As with all medicines, especially ones in liquid form, care should be taken in handling NICOTROL NS during periods of opening and closing the container (See WARNINGS and Safety Note Concerning Children). If it is dropped it may break. If this occurs, the spill should be cleaned up immediately with an absorbent cloth/paper towel. Care should be taken to avoid contact of the solution with the skin. Broken glass should be picked up carefully, using a broom. The area of the spill should be washed several times. Absorbent material may be disposed of as any other household waste. Should even a small amount of NICOTROL NS come in contact with the skin, lips, mouth, eyes or ears, the affected area(s) should be immediately rinsed with water only.

Disposal

Used bottles of NICOTROL NS should be disposed of with their child-resistant caps in place. Used bottles should be disposed of in such a way as to prevent access by children or pets. See patient information for further information on handling and disposal.

How Supplied

NICOTROL® NS (nicotine nasal spray) 10 mg/mL, is supplied as four 10 mL bottles (NDC 0009-5401-01). Each unit consists of a glass container, mounted with a metered spray pump.
A patient information leaflet is enclosed with the package.

Store at 25°C (77°F); excursions permitted to 15° to 30°C (59° to 86°F) [see USP Controlled Room Temperature].

Rx only

LAB-0677-5.0
Revised June 2024

Nicotrol®NS (nicotine nasal spray)

An Aid To Help You Stop Smoking

PATIENT INFORMATION

Read and follow carefully. If you have questions or want more information, ask your doctor or pharmacist.

IMPORTANT INFORMATION—Read carefully

1. NICOTROL® NS Nasal Spray is designed to help you quit smoking by reducing your urge to smoke. What causes the urge to smoke? It is the nicotine in cigarettes. NICOTROL® NS contains nicotine. Your doctor may increase or decrease dosage during the first few weeks. As your body adjusts to not smoking, your doctor will either tell you to stop using NICOTROL® NS or gradually reduce your dose.
  1. People who use NICOTROL® NS with a comprehensive behavioral smoking cessation program are more successful in quitting smoking. This program can include support groups, counseling or specific behavior change techniques.
2. Side Effects—During the first week or so most people experience the following side effects: hot, peppery feeling in back of throat or nose, sneezing, coughing, watery eyes, or runny nose. Wait 5 minutes before driving. Be sure to use regularly for the first week to help adjust to the side effects.
3. Because nicotine is addictive, it is possible to become dependent on the Nasal Spray. It is important to use the Nasal Spray only for as long as needed to overcome your smoking habit (as directed by your doctor). Your chance of becoming dependent on the Nasal Spray increases if you use it longer than 6 months.

WARNINGS—Read before using NICOTROL® NS

1. Commit yourself—NO SMOKING! For NICOTROL® NS to help, you must be firmly committed to quitting! Stop smoking as soon as you start using NICOTROL® NS. Do not smoke or use any other tobacco product at any time while under treatment with NICOTROL® NS—nicotine overdose can occur. If symptoms of overdose occur, call a doctor or Poison Control Center.
  Nicotine overdose symptoms include:

- bad headaches
- dizziness
- upset stomach

- drooling
- vomiting
- diarrhea

- cold sweat
- weak and irregular pulse
- blurred vision

- hearing difficulties
- mental confusion
- weakness and fainting

2. Keep out of reach of children and pets. NICOTROL® NS can cause serious illness in children and pets—even in very small amounts. If a child uses or handles NICOTROL® NS, call a doctor or Poison Control Center. When the bottle is empty, replace cap and throw away out of reach of children and pets. Even empty bottles contain enough nicotine to seriously harm children and pets.
3. Tell your doctor if you have:

- chronic nasal problems such as
  nasal allergies, inflammation,
  sinusitis or nasal polyps (growths)
- heart problems (recent heart attack, irregular heartbeat, severe or worsening heart pain)
- high blood pressure

- drug allergies
- stomach ulcers or heartburn
- wheezing or asthma
- overactive thyroid
- diabetes requiring insulin
- kidney or liver disease

Tell your doctor about any medicines you are taking—the dosages may need to be changed. Check with your doctor before taking any new medicine while using NICOTROL® NS.

4. If you are pregnant or breast-feeding, only use this medicine on the advice of your health care provider. Smoking can seriously harm your child. Try to stop smoking without using any nicotine replacement medicine. This medicine is believed to be safer than smoking. However, the risks to your child from this medicine are not fully known.

FOLLOW DIRECTIONS

BEFORE YOU USE — Read information on both sides

BEFORE YOU USE—Read information on both sides

FOLLOW DOSAGE:

WHAT TO EXPECT (First Week):

- Use as directed by doctor.
- But do not use more than 5 times an hour or 40 times in 24 hours.
- Stop smoking completely during NICOTROL® NS treatment program.

- Hot, peppery feeling in back of throat or nose, sneezing, coughing, watery eyes, or runny nose.
- To Help Adjust to Spray—use regularly for first week.
- Side effects will lessen for most people in a few days—don't stop using the Nasal Spray. If side effects do not lessen after a week, call your doctor.

REMOVE CAP:

PRIME PUMP (before first use):

- Press in circles on sides of bottle.
- Pull off cap as shown.

- Get a tissue or paper towel.
- Hold bottle as shown.
- Press up on bottom with thumb.
- Pump into tissue until you see a fine spray (6 to 8 times).
- Throw tissue away.

FOLLOW DIRECTIONS EXACTLY — Questions? (call 1-888-642-6876)

- Blow nose if it is not clear.
- Tilt head back slightly.
- Hold bottle as shown.

- Insert tip of bottle into nostril—as far as is comfortable.
- Breathe through mouth.
- Spray once in each nostril. Do not sniff or inhale while spraying.
- If nose runs, gently sniff to keep the Nasal Spray in nose. Wait 2 or 3 minutes before blowing nose.

AVOID contact with skin, eyes, and mouth. If bottle breaks, wear rubber gloves, wipe up with paper towel and wash surfaces thoroughly. Do not let nicotine come in contact with your skin, mouth, or eyes. If it does, rinse with plain water immediately. Nicotine overdose can occur when nicotine is absorbed through the skin. If symptoms of overdose occur (see other side for symptoms), call a doctor or Poison Control Center.

- Place cap back on bottle after use.
- Store at room temperature, 59°F to 86°F (15°C to 30°C), out of reach of children.
- If you don't use the Nasal Spray for 24 hours, prime pump in tissue 1 or 2 times.
- Most vials of NICOTROL® NS contain 100 doses (200 sprays), but excessive priming will reduce the amount of medicine available for use. Avoid excessive priming.

LAB-0344-7.0
Revised June 2024

PRINCIPAL DISPLAY PANEL - 10 mg/mL Bottle Label

NDC 0009-5401-01

Nicotrol® NS
(nicotine
nasal spray)

10 mg/mL

FOR NASAL USE ONLY
KEEP OUT OF REACH OF CHILDREN

10 mL

Rx only

PRINCIPAL DISPLAY PANEL - 10 mg/mL Bottle Box

NDC 0009-5401-01

Nicotrol® NS
(nicotine
nasal spray

10 mg/mL

Pharmacist: Place prescription label here.
This package contains prescribing information which includes patient instructions.